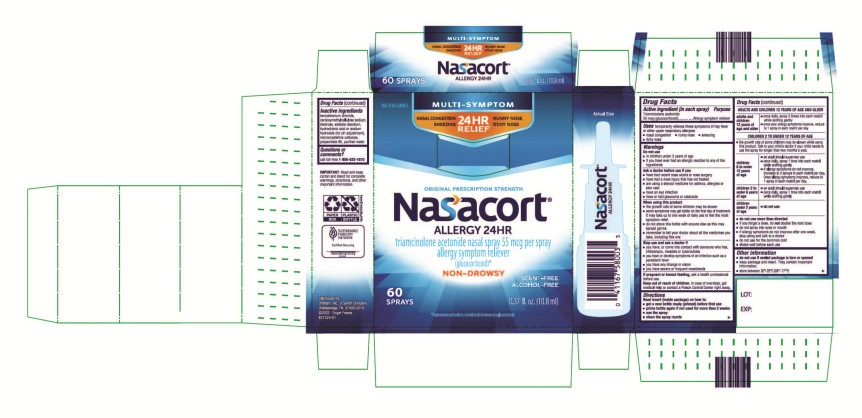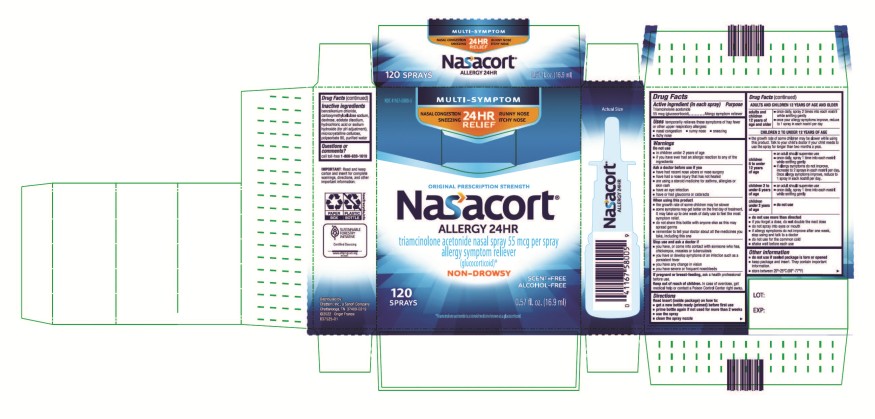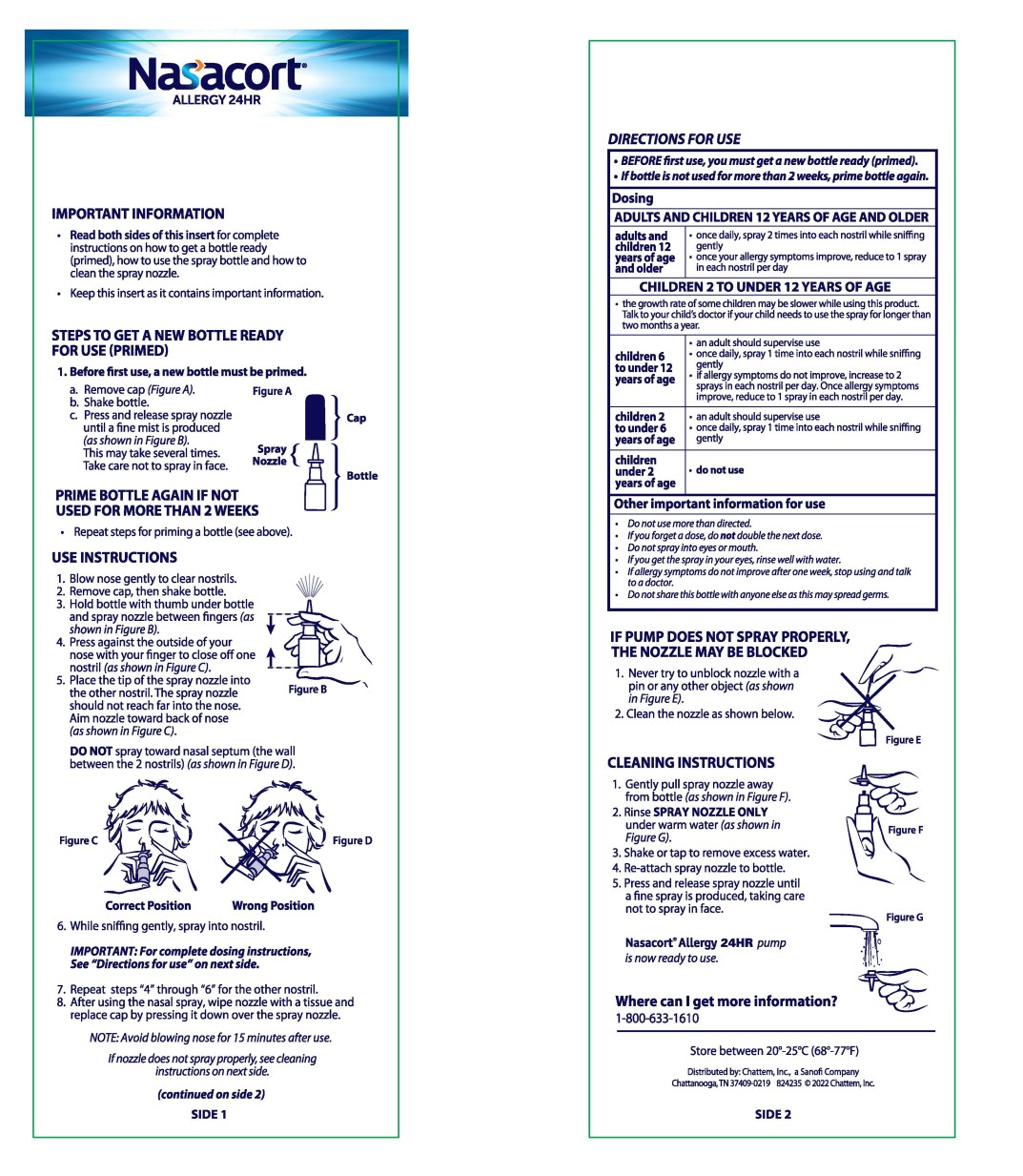 DRUG LABEL: Nasacort Allergy 24HR
NDC: 41167-5800 | Form: SPRAY, METERED
Manufacturer: Chattem, Inc.
Category: otc | Type: HUMAN OTC DRUG LABEL
Date: 20260114

ACTIVE INGREDIENTS: TRIAMCINOLONE ACETONIDE 55 ug/1 1
INACTIVE INGREDIENTS: CELLULOSE, MICROCRYSTALLINE; CARBOXYMETHYLCELLULOSE SODIUM; POLYSORBATE 80; DEXTROSE; BENZALKONIUM CHLORIDE; EDETATE DISODIUM; HYDROCHLORIC ACID; SODIUM HYDROXIDE; WATER

Nasacort Allergy 24HR

Nasacort Allergy 24HR

Drug Facts

Active ingredient

(in each spray)

Triamcinolone acetonide

55 mcg (glucocorticoid)

Purpose

Allergy symptom reliever

Uses

temporarily relieves these symptoms of hay fever or other upper
respiratory allergies:

- nasal congestion
- runny nose
- sneezing
- itchy nose

Warnings

Do not use

- in children under 2 years of age
- if you have ever had an allergic reaction to any of the ingredients

Ask a doctor before use if you

- have had recent nose ulcers or nose surgery
- have had a nose injury that has not healed
- are using a steroid medicine for asthma, allergies or skin rash
- have an eye infection
- have or had glaucoma or cataracts

When using this product

- the growth rate of some children may be slower
- some symptoms may get better on the first day of treatment. It may take up to one week of daily use to feel the most symptom relief.
- do not share this bottle with anyone else as this may spread germs
- remember to tell your doctor about all the medicines you take, including this one

Stop use and ask a doctor if

- you have, or come into contact with someone who has, chickenpox, measles or tuberculosis
- you have or develop symptoms of an infection such as a persistent fever
- you have any change in vision
- you have severe or frequent nosebleeds

If pregnant or breast-feeding,

ask a health professional before use.

Keep out of reach of children.

In case of overdose, get medical help or contact a Poison Control Center right away.

Directions

Read insert (inside package) on how to:

- get a new bottle ready (primed) before first use
- prime bottle again if not used for more than 2 weeks
- use the spray
- clean the spray nozzle

ADULTS AND CHILDREN 12 YEARS OF AGE AND OLDER
adults and children 12 years of age and older | - once daily, spray 2 times into each nostril while sniffing gently - once your allergy symptoms improve, reduce to 1 spray in each nostril per day
CHILDREN 2 TO UNDER 12 YEARS OF AGE
- the growth rate of some children may be slower while using this product. Talk to your child’s doctor if your child needs to use the spray for longer than two months a year.
children 6 to under 12 years of age | - an adult should supervise use - once daily, spray 1 time into each nostril while sniffing gently - if allergy symptoms do not improve, increase to 2 sprays in each nostril per day. Once allergy symptoms improve, reduce to 1 spray in each nostril per day.
children 2 to under 6 years of age | - an adult should supervise use - once daily, spray 1 time into each nostril while sniffing gently
children under 2 years of age | - do not use

- do not use more than directed
- if you forget a dose, do not double the next dose
- do not spray into eyes or mouth
- if allergy symptoms do not improve after one week, stop using and talk to a doctor
- do not use for the common cold
- shake well before each use

Other information

- do not use if sealed package is torn or opened
- keep package and insert. They contain important information.
- store between 20°- 25°C (68°-77°F)

Inactive ingredients

benzalkonium chloride, carboxymethylcellulose sodium, dextrose, edetate disodium, hydrochloric acid or sodium hydroxide (for pH adjustment), microcrystalline cellulose, polysorbate 80, purified water

Questions or comments?

call toll-free 1-800-633-1610

Principal Display Panel

NDC 41167-5800-3
Multi-Symptom
Nasal Allergy Spray
Nasacort
Allergy 24HR
triamcinolone acetonide nasal spray 55 mcg per spray
allergy symptom reliever
(glucocorticoid)*
0.37 fl. oz. (10.8 ml) 60 Sprays

*Triamcinolone acetonide
is a steroid medicine
known as a glucocorticoid.

Principal Display Panel

Original Prescription Strength
NDC 41167-5800-5
Multi-Symptom
Nasal Allergy Spray
Nasacort
Allergy 24HR
triamcinolone acetonide nasal spray 55 mcg per spray
allergy symptom reliever
(glucocorticoid)*
0.57 fl. oz. (16.9 ml) 120 Sprays

*Triamcinolone acetonide
is a steroid medicine
known as a glucocorticoid.

Principal Display Panel

Nasacort Allergy 24HR
Multi-Symptom
Nasal Allergy Spray
Insert